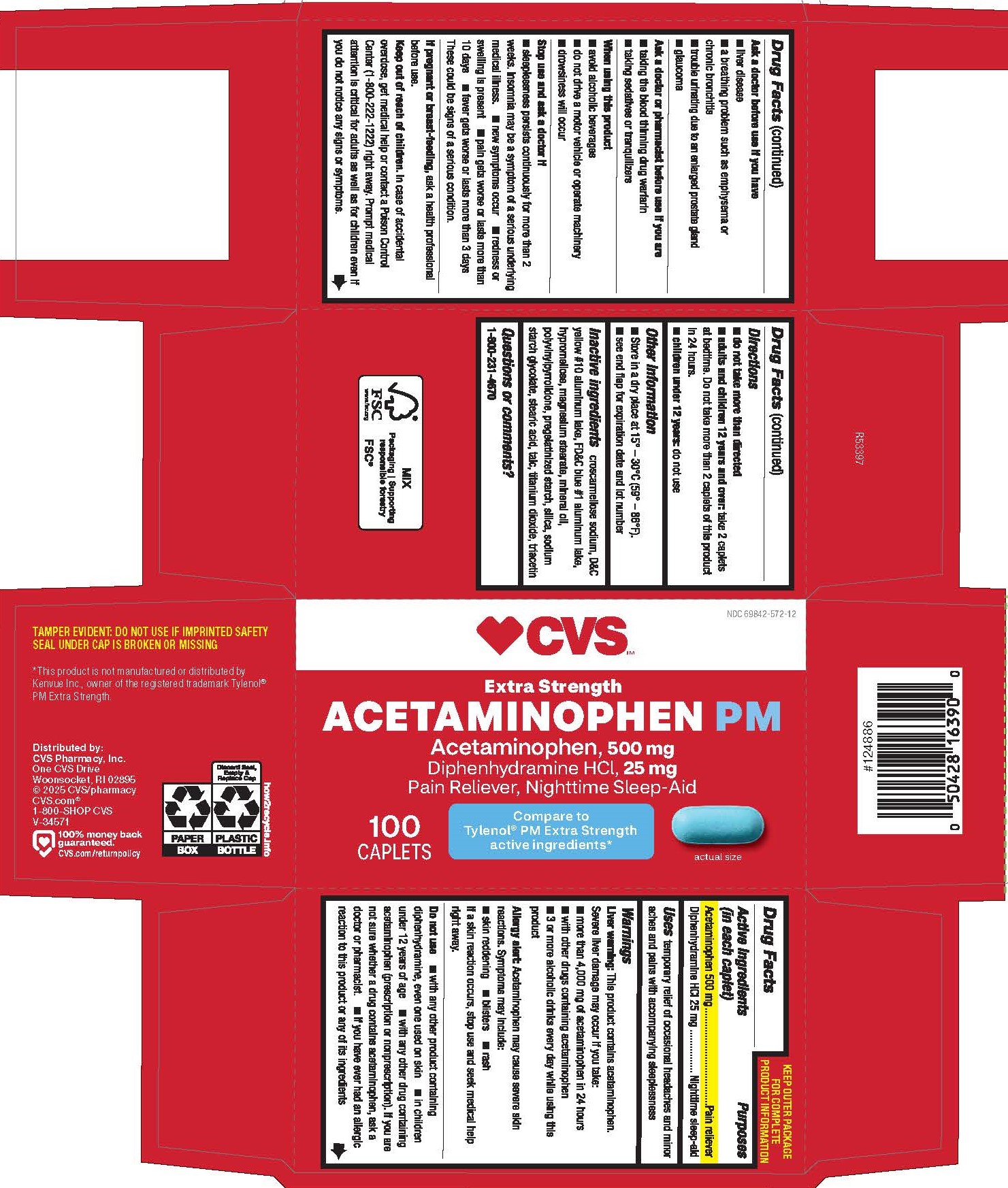 DRUG LABEL: ACETAMINOPHEN, DIPHENHYDRAMINE HCL
NDC: 69842-572 | Form: TABLET, FILM COATED
Manufacturer: CVS Pharmacy, Inc.
Category: otc | Type: HUMAN OTC DRUG LABEL
Date: 20250611

ACTIVE INGREDIENTS: DIPHENHYDRAMINE HYDROCHLORIDE 25 mg/1 1; ACETAMINOPHEN 500 mg/1 1
INACTIVE INGREDIENTS: TRIACETIN; MAGNESIUM STEARATE; POVIDONE K30; TALC; FD&C BLUE NO. 1; CROSCARMELLOSE SODIUM; D&C YELLOW NO. 10; SILICON DIOXIDE; LIGHT MINERAL OIL; STARCH, PREGELATINIZED CORN; SODIUM STARCH GLYCOLATE TYPE A POTATO; STEARIC ACID; TITANIUM DIOXIDE; HYPROMELLOSES

0752-CVS

Drug Facts

Active ingredients (in each caplet)

Acetaminophen 500 mg

Diphenhydramine HCl 25 mg

Purpose

Pain reliever and Nighttime sleep-aid

Uses

temporary relief of occasional headaches and minor aches and pains with accompanying sleeplessness

WARNINGS

Liver warning: This product contains acetaminophen. Severe liver damage may occur if you take:

- more than 4,000 mg of acetaminophen in 24 hours
- with other drugs containing acetaminophen
- 3 or more alcoholic drinks every day while using this product

Allergy alert: Acetaminophen may cause severe skin reactions. Symptoms may include:

- skin reddening
- blisters
- rash

If a skin reaction occurs, stop use and seek medical help right away.

Do not use

- with any other product containing diphenhydramine, even one used on skin
- in children under 12 years of age
- with any other drug containing acetaminophen (prescription or nonprescription). If you are not sure whether a drug contains acetaminophen, ask a doctor or pharmacist.
- if you have ever had an allergic reaction to this product or any of its ingredients

Ask a doctor before use if you have

- liver disease
- a breathing problem such as emphysema or chronic bronchitis
- trouble urinating due to an enlarged prostate gland
- glaucoma

Ask a doctor or pharmacist before use if you are

- taking the blood thinning drug warfarin
- taking sedatives or tranquilizers

When using this product

- avoid alcoholic beverages
- do not drive a motor vehicle or operate machinery
- drowsiness will occur

Stop use and ask a doctor if

- sleeplessness persists continuously for more than 2 weeks. Insomnia may be a symptom of a serious underlying medical illness.
- new symptoms occur
- redness or swelling is present
- pain gets worse or lasts more than 10 days
- fever gets worse or lasts more than 3 days

These could be signs of a serious condition.

PREGNANCY OR BREAST FEEDING

If pregnant or breast-feeding,ask a health professional before use.

Keep out of reach of children.

OVERDOSAGE

In case of accidental overdose, get medical help or contact a Poison Control Center (1-800-222-1222) right away. Prompt medical attention is critical for adults as well as for children even if you do not notice any signs or symptoms.

Directions

- do not take more than directed
- adults and children 12 years and over: take 2 caplets at bedtime. Do not take more than 2 caplets of this product in 24 hours.
- children under 12 years: do not use

Other information

- Store in a dry place at 15°-30°C (59°-86°F).
- see end flap for expiration date and lot number

INACTIVE INGREDIENT

croscarmellose sodium, D&C yellow #10 aluminum lake, FD&C blue #1 aluminum lake, hypromellose, magnesium stearate, mineral oil, polyvinylpyrrolidone, pregelatinized starch, silica, sodium starch glycolate, stearic acid, talc, titanium dioxide, triacetin

Questions or comments?

1-800-231-4670

TAMPER EVIDENT: DO NOT USE IF IMPRINTED SAFETY SEAL UNDER CAP IS BROKEN OR MISSING

*This product is not manufactured or distributed by Kenvue Inc., owner of the registered trademark Tylenol® PM Extra Strength.

Distributed by: CVS Pharmacy, Inc.

One CVS Drive

Woonsocket, RI 02895

© 2025 CVS/pharmacy

CVS.com® 1-800-SHOP CVS

V-34571

PACKAGE LABEL

CVS

NDC 69842-572-12

Extra Strength

ACETAMINOPHEN PM

Acetaminophen, 500 mg

Diphenhydramine HCl, 25 mg

Pain Reliever, Nighttime Sleep-Aid

Compare to Tylenol® PM Extra Strength active ingredients*

100 CAPLETS